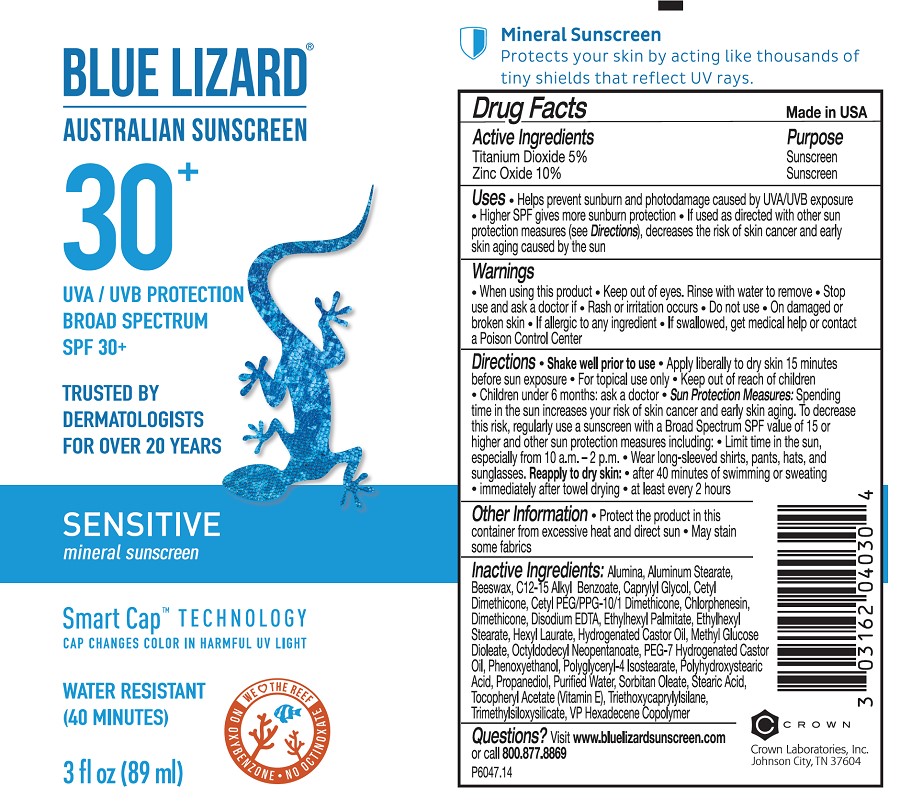 DRUG LABEL: Blue Lizard Sensitive Sunscreen
NDC: 0316-2045 | Form: LOTION
Manufacturer: Crown Laboratories
Category: otc | Type: HUMAN OTC DRUG LABEL
Date: 20260112

ACTIVE INGREDIENTS: TITANIUM DIOXIDE 54 mg/1 mL; ZINC OXIDE 108 mg/1 mL
INACTIVE INGREDIENTS: ETHYLHEXYL PALMITATE; ETHYLHEXYL STEARATE; CAPRYLYL GLYCOL; HEXYL LAURATE; HYDROGENATED CASTOR OIL; METHYL GLUCOSE DIOLEATE; CHLORPHENESIN; OCTYLDODECYL NEOPENTANOATE; PEG-7 HYDROGENATED CASTOR OIL; POLYGLYCERYL-4 ISOSTEARATE; PHENOXYETHANOL; PROPANEDIOL; WATER; SORBITAN MONOOLEATE; STEARIC ACID; .ALPHA.-TOCOPHEROL ACETATE; HEXADECYL POVIDONE (4 HEXADECYL BRANCHES/REPEAT); DIMETHICONE; TRIMETHYLSILOXYSILICATE (M/Q 0.8-1.0); CETYL DIMETHICONE 25; POLYHYDROXYSTEARIC ACID (2300 MW); ALUMINUM STEARATE; TRIETHOXYCAPRYLYLSILANE; ALUMINUM OXIDE; YELLOW WAX; ALKYL (C12-15) BENZOATE; CETYL PEG/PPG-10/1 DIMETHICONE (HLB 5); EDETATE DISODIUM

Blue Lizard Sensitive

Active Ingredients

Titanium Dioxide 5%

Zinc Oxide 10%

Purpose

Sunscreen

Uses

- Helps prevent sunburn and photodamage caused by UVA/UVB exposure
- Higher SPF gives more sunburn protection
- If used as directed with other sun protection measures (see Directions), decreases the risks of skin cancer and early skin aging caused by the sun

Warnings

- When using this product
- Keep out of eyes. Rinse with water to remove
- Stop use and ask doctor if
- Rash or irritation occurs
- Do not use
- On damaged or broken skin
- If allergic to any ingredient
- If swallowed, get medical help or contact a Poison Control Center

Directions

- Shake well prior to use
- Apply liberally to dry skin 15 minutes before sun exposure
- For topical use only
- Children under 6 months of age: ask a doctor
- Sun Protection Measures: Spending time in the sun increases your risk of skin cancer and early skin aging. To decrease this risk, regularly use a sunscreen with a Broad Spectrum SPF value of 15 or higher and other sun protection measures including:
- Limit time in the sun especially from 10 a.m.- 2 p.m.
- Wear long-sleeved shirts, pants, hats, and sunglasses
- Reapply to dry skin:
- after 40 minutes of swimming or sweating
- immediately after towel drying
- at least every 2 hours

Other Information

- Protect the product in this container from excessive heat and direct sun
- May stain some fabrics

Inactive Ingredients

Alumina, Aluminum Stearate, Beeswax, C12-15 Alkyl Benzoate, Caprylyl Glycol, Cetyl Dimethicone, Cetyl PEG/PPG-10/1 Dimethicone, Chlorphenesin, Dimethicone, Disodium EDTA, Ethylhexyl Palmitate, Ethylhexyl Stearate, Hexyl Laurate, Hydrogenated Castor Oil, Methyl Glucose Dioleate, Octyldodecyl Neopentanoate, PEG-7 Hydrogenated Castor Oil, Phenoxyethanol, Polyglyceryl-4 Isostearate, Polyhydroxystearic Acid, Propanediol, Purified Water, Sorbitan Oleate, Stearic Acid, Tocopheryl Acetate (Vitamin E), Triethoxycaprylylsilane, Trimethylsiloxysilicate, VP Hexadecene Copolymer

Questions?

Visit www.bluelizardsunscreen.com or call 800.877.8869

Crown Laboratories, Inc., Johnson City, TN 37604

RECENT MAJOR CHANGES

Formatted Uses section

Formatted Directions section

Prinicipal Display Panel

BLUE LIZARD

AUSTRALIAN SUNSCREEN

30+

UVA/UVB PROTECTION

BROAD SPECTRUM

SPF 30+

TRUSTED BY DERMATOLOGISTS FOR OVER 20 YEARS

SENSITIVE

Mineral Sunscreen

Smart Cap TECHNOLOGY

CAP CHANGES COLOR IN HARMFUL UV LIGHT

WATER RESISTANT (40 MINUTES)

Mineral Sunscreen

Protects your skin by acting like thousands of tiny shields that reflect UV rays.

3fl oz (89ml)

P6047.14